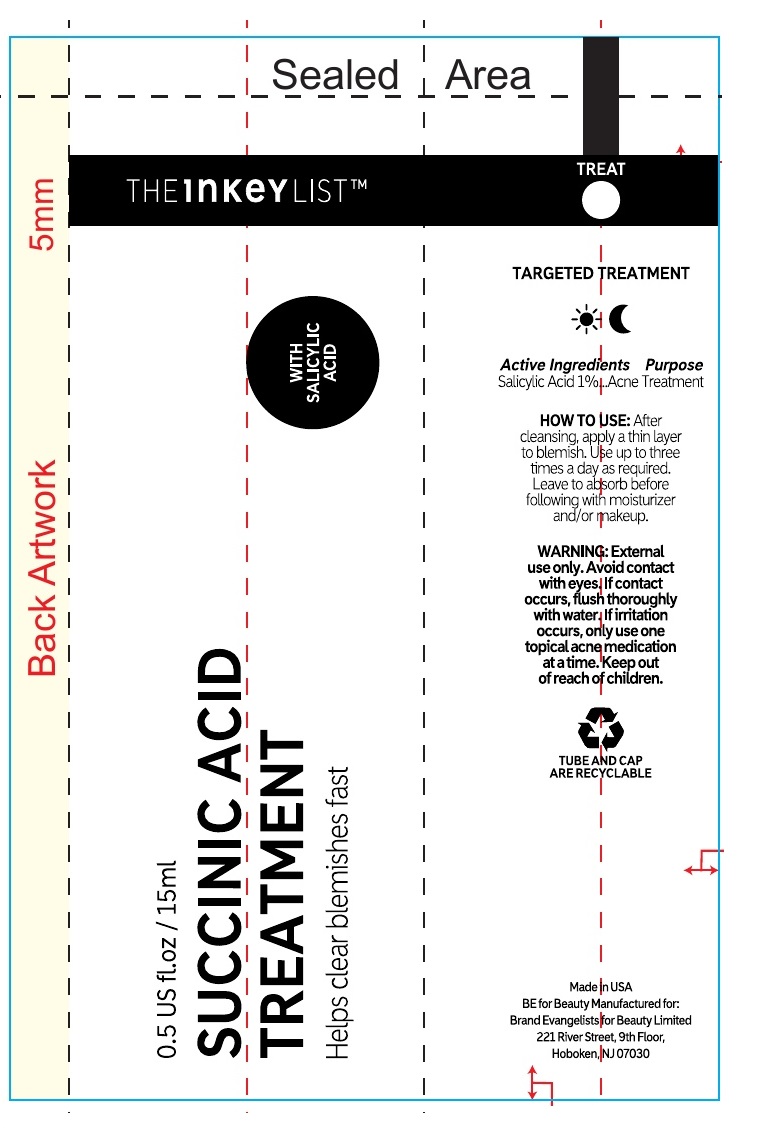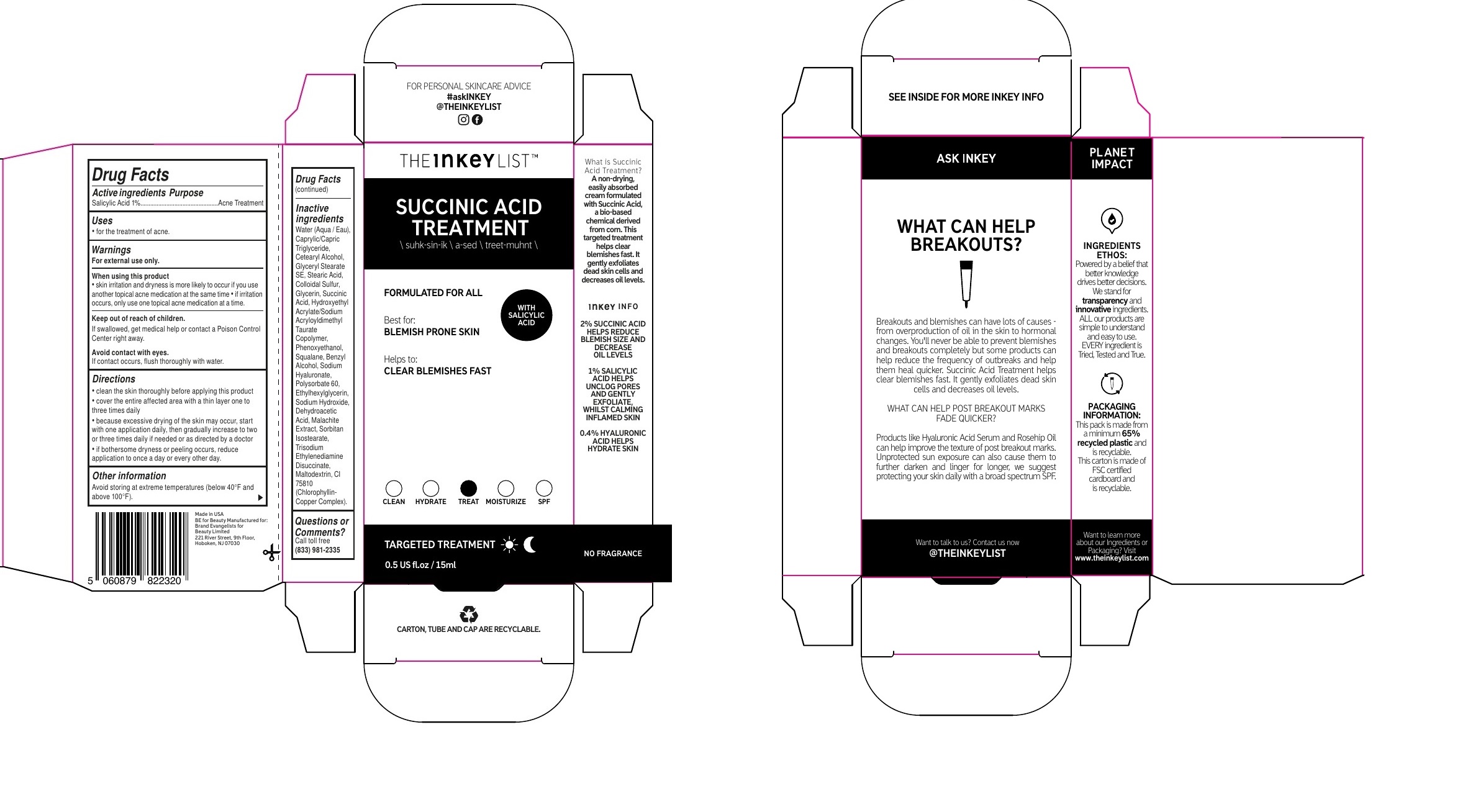 DRUG LABEL: THE INKEY LIST SUCCINIC ACID ACNE TREATMENT
NDC: 81136-017 | Form: CREAM
Manufacturer: Brand Evangelists for Beauty Ltd
Category: otc | Type: HUMAN OTC DRUG LABEL
Date: 20240226

ACTIVE INGREDIENTS: SALICYLIC ACID 10 mg/1 mL
INACTIVE INGREDIENTS: WATER; MEDIUM-CHAIN TRIGLYCERIDES; GLYCERYL STEARATE SE; STEARIC ACID; CETOSTEARYL ALCOHOL; SULFUR; GLYCERIN; SUCCINIC ACID; HYDROXYETHYL ACRYLATE/SODIUM ACRYLOYLDIMETHYL TAURATE COPOLYMER (100000 MPA.S AT 1.5%); PHENOXYETHANOL; SQUALANE; BENZYL ALCOHOL; HYALURONATE SODIUM; POLYSORBATE 60; ETHYLHEXYLGLYCERIN; SODIUM HYDROXIDE; DEHYDROACETIC ACID; SORBITAN ISOSTEARATE; TRISODIUM ETHYLENEDIAMINE DISUCCINATE; SODIUM COPPER CHLOROPHYLLIN

THE INKEY LIST- SUCCINIC ACID ACNE TREATMENT

Active ingredients

Salicylic Acid 1%

Purpose

Acne Treatment

Uses

- for the treatment of acne.

Warnings

For external use only.

When using this product

• skin irritation and dryness is more likely to occur if you use another topical acne medication at the same time • if irritation occurs, only use one topical acne medication at a time.

Keep out of reach of children.

If swallowed, get medical help or contact a Poison Control Center right away.

If contact occurs, flush thoroughly with water. Avoid contact with eyes.

Directions

• clean the skin thoroughly before applying this product • cover the entire affected area with a thin layer one to three times daily • because excessive drying of the skin may occur, start with one application daily, then gradually increase to two or three times daily if needed or as directed by a doctor • if bothersome dryness or peeling occurs, reduce application to once a day or every other day.

Other information

Avoid storing at extreme temperatures (below 40°F and above 100°F).

Inactive ingredients

Water, Caprylic/Capric Triglyceride, Glyceryl Stearate SE, Stearic Acid, Cetearyl Alcohol, Colloidal Sulfur, Glycerin, Succinic Acid, Hydroxyethyl Acrylate/Sodium Acryloyldimethyl Taurate Copolymer, Phenoxyethanol, Squalane, Benzyl Alcohol, Sodium Hyaluronate, Polysorbate 60, Ethylhexylglycerin, Sodium Hydroxide, Dehydroacetic Acid, Malachite Extract, Sorbitan Isostearate, Trisodium Ethylenediamine Disuccinate, CI 75810 (Chlorophyllin-Copper Complex).

Questions or Comments?

Call toll free (833) 981-2335